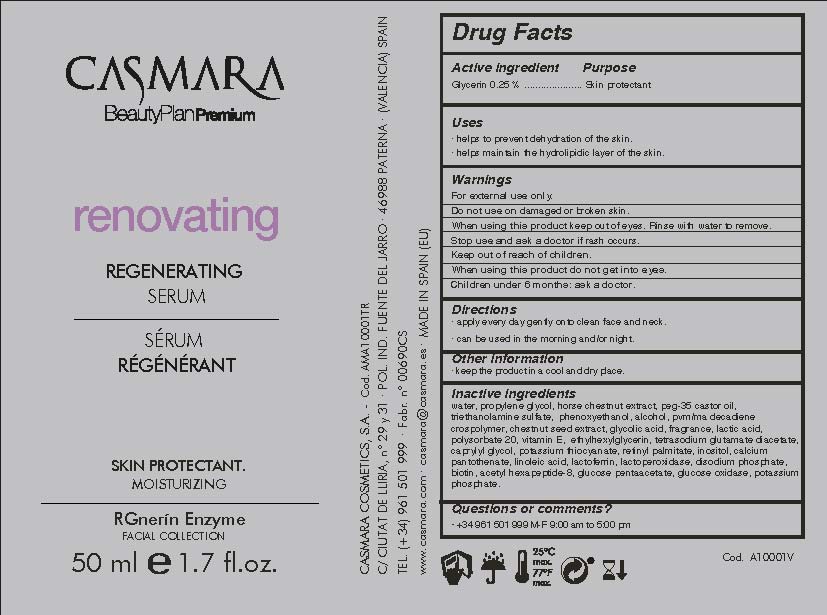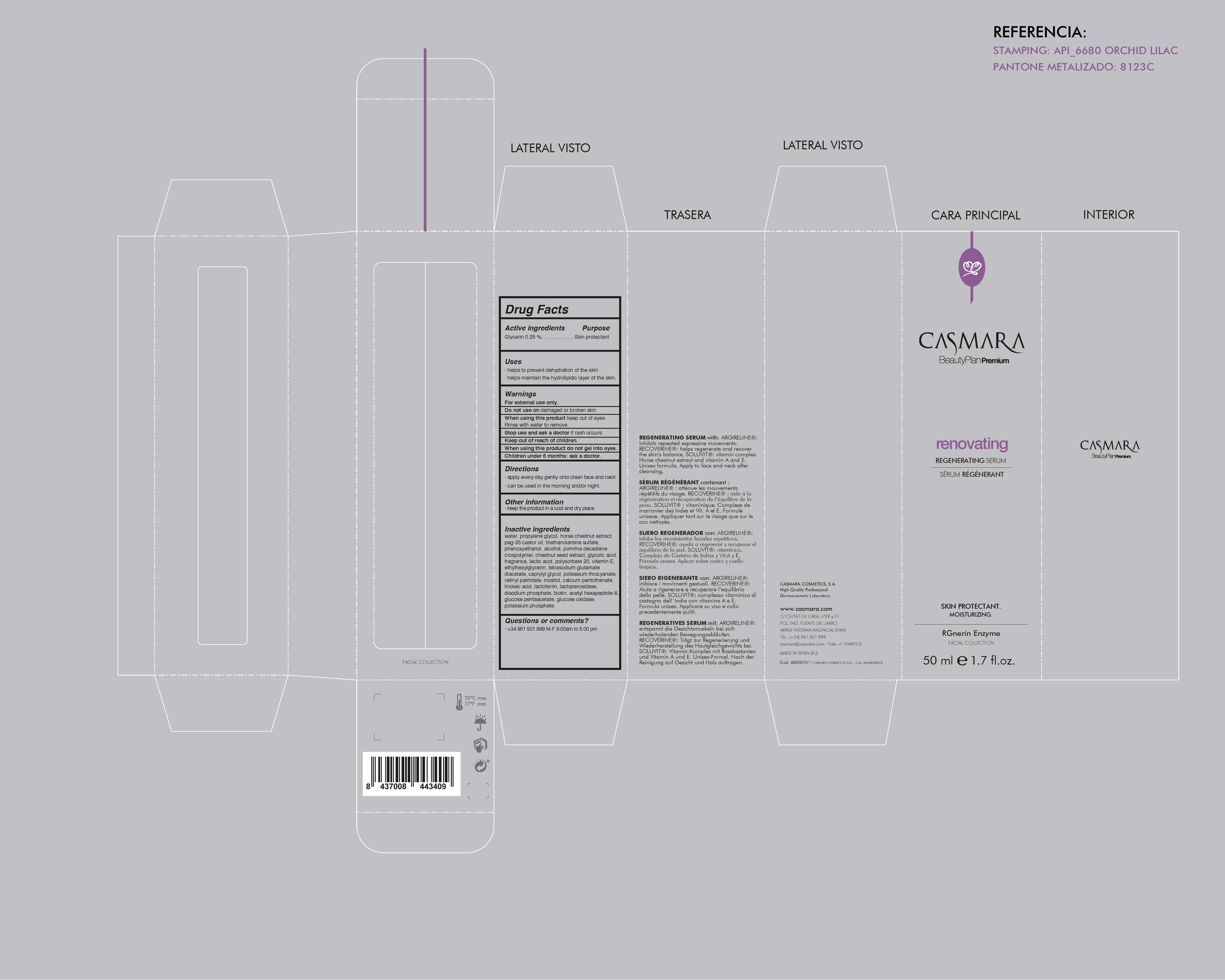 DRUG LABEL: Renovating Regenerating Serum
NDC: 20151-068 | Form: CREAM
Manufacturer: Casmara Cosmetics, SA
Category: otc | Type: HUMAN OTC DRUG LABEL
Date: 20161101

ACTIVE INGREDIENTS: GLYCERIN 0.25 mg/1 mL
INACTIVE INGREDIENTS: POLYOXYL 35 CASTOR OIL 1.875 mg/1 mL; BUTYL ESTER OF METHYL VINYL ETHER-MALEIC ANHYDRIDE COPOLYMER (125 KD) 0.8 mg/1 mL; HORSE CHESTNUT 0.3 mg/1 mL; POLYSORBATE 20 0.15 mg/1 mL; LINOLEIC ACID 0.027 mg/1 mL; LACTOPEROXIDASE BOVINE 0.015 mg/1 mL; BIOTIN 0.005 mg/1 mL; CALCIUM PANTOTHENATE, (-)- 0.027 mg/1 mL; POTASSIUM THIOCYANATE 0.037 mg/1 mL; LACTOFERRIN, BOVINE 0.025 mg/1 mL; GLUCOSE PENTAACETATE 0.0035 mg/1 mL; GLUCOSE OXIDASE 0.001 mg/1 mL; VITAMIN A PALMITATE 0.027 mg/1 mL; SPANISH CHESTNUT 1.875 mg/1 mL; GLYCOLIC ACID 0.21 mg/1 mL; CAPRYLYL GLYCOL 0.05 mg/1 mL; ETHYLHEXYLGLYCERIN 0.106 mg/1 mL; WATER 72.75 mg/1 mL; PHENOXYETHANOL 0.915 mg/1 mL; TETRASODIUM GLUTAMATE DIACETATE 0.094 mg/1 mL; TOCOPHEROL 0.15 mg/1 mL; PERFLUNAFENE 0.2 mg/1 mL; POTASSIUM PHOSPHATE, MONOBASIC 0.001 mg/1 mL; TROLAMINE 1 mg/1 mL; DIPROPYLENE GLYCOL 18 mg/1 mL; SODIUM PHOSPHATE 0.0115 mg/1 mL; INOSITOL 0.0275 mg/1 mL; ALCOHOL 0.875 mg/1 mL; ACETYL HEXAPEPTIDE-8 0.005 mg/1 mL; LACTIC ACID 0.18 mg/1 mL

Renovating Regenerating Serum.

WARNINGS

For external use only.

Do not use on damaged or broken skin.

When using this product keep our of the eyes. Rinse with water to remove.

Stop use and ask a doctor if rash occurs.

Keep out of reach of children.

Whhen using this product do not get into eyes.

Children under 6 months: as a doctor.

Stop use and ask a doctor if rash occurs

Children under 6 months: ask a doctor

. keep out of reach of children

Questions or comments? + 34 961 501 099 M-F 9:00 am to 5:00 pm

OTHER SAFETY INFORMATION

. keep the product in a cool and dry place

Directions

. apply every day gently onto clean face and neck

. can be used in the morning and/or night

DOSAGE AND ADMINISTRATION

. apply every day gently onto clean dace and neck

. can be used in the morning and/or night

Uses

. helps to prevent dehydration of the skin.

. helps maintain the hydrolipidic layer of the skin

INACTIVE INGREDIENT

water, propylene glycol, horse chestnut extract, PEG-25 castor oil, triethanolamine, phenoxyethanol, alcohol, PVM/MA Decadiene crospolymer, chestnut seed extract, glycolic acid, fragrance, lactic acid, polysorbate 20, tocopherol, ethylhexylglycerin, tetrasodium glutamate diacetate, caprylyl glycol, potassium thiocyanate, retinyl palmitate, inositol, calcium pantothenate, linoleic acid, lactoferrin, lactoperoxidase, disodium phosphate, biotin, acetyl hexapeptide-8, glucose pentaacetate, glucose oxidase, potassium phosphate

PURPOSE

. helps to prevent dehydration of the skin

. helps maintain the hydrolipidic layer of the skin

Active Ingredients

Glycerin 0.25%........................... Skin Protectant

PACKAGE LABEL

Renovating

Regenerating Serum

Skin Protectant

Moisturizing

RGnerin Enzyme

Facial Collection